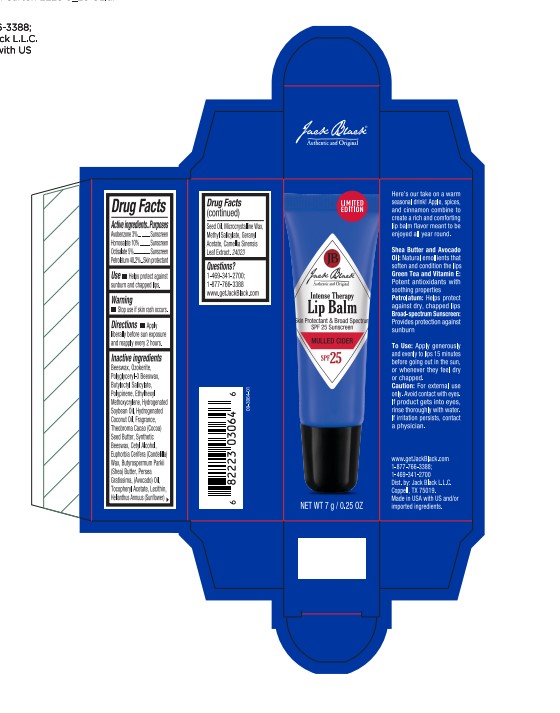 DRUG LABEL: Jack Black
NDC: 66738-161 | Form: OINTMENT
Manufacturer: Jack Black L.L.C.
Category: otc | Type: HUMAN OTC DRUG LABEL
Date: 20250905

ACTIVE INGREDIENTS: PETROLATUM 40.2 g/100 mL; AVOBENZONE 3 g/100 mL; HOMOSALATE 5 g/100 mL; OCTISALATE 5 g/100 mL
INACTIVE INGREDIENTS: ETHYLHEXYL METHOXYCRYLENE; CETYL ALCOHOL; HELIANTHUS ANNUUS (SUNFLOWER) SEED OIL; SYNTHETIC BEESWAX; .ALPHA.-TOCOPHEROL ACETATE; BUTYROSPERMUM PARKII (SHEA) BUTTER; GERANYL ACETATE; CAMELLIA SINENSIS LEAF; BEESWAX; POLYGLYCERYL-3 BEESWAX; PERSEA GRATISSIMA (AVOCADO) OIL; MICROCRYSTALLINE WAX; HYDROGENATED SOYBEAN OIL; HYDROGENATED COCONUT OIL; EUPHORBIA CERIFERA (CANDELILLA) WAX; CERESIN; BUTYLOCTYL SALICYLATE; METHYL SALICYLATE; THEOBROMA CACAO (COCOA) SEED BUTTER

ACTIVE INGREDIENT

Avobenzone 3%
Homosalate 10%
Octisalate 5%
Petrolatum 40.2%

Purposes

Sunscreen

Sunscreen

Sunscreen

Skin protectant

Use

• Helps protect against sunburn and chapped lips.

Warning

Stop use if skin rash occurs.

Keep out of reach of children.

Directions

• Apply liberally before sun exposure and reapply every 2 hours.

Inactive ingredients

Beeswax, Ozokerite, Polyglyceryl-3 Beeswax, Butyloctyl Salicylate, Polypinene, Ethylhexyl Methoxycrylene, Hydrogenated Soybean Oil, Hydrogenated Coconut Oil, Fragrance, Theobroma Cacao (Cocoa) Seed Butter, Synthetic Beeswax, Cetyl Alcohol, Euphorbia Cerifera (Candelilla) Wax, Butyrospermum Parkii (Shea) Butter, Persea Gratissima (Avocado) Oil, Tocopheryl Acetate, Lecithin, Helianthus Annuus (Sunflower) Seed Oil, Microcrystalline Wax, Methyl Salicylate, Geranyl Acetate, Camellia Sinensis Leaf Extract.

Questions?

1-469-341-2700; 1-877-766-3388 www.getJackBlack.com